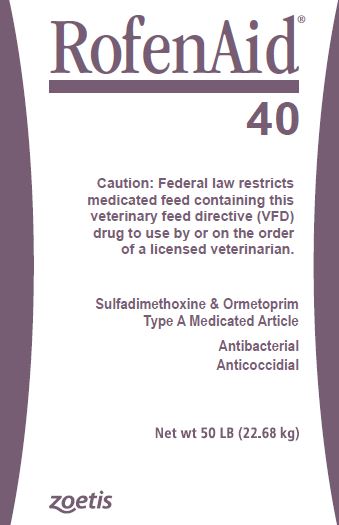 DRUG LABEL: Rofenaid 40
NDC: 54771-1446 | Form: POWDER
Manufacturer: Zoetis Inc.
Category: animal | Type: VFD TYPE A MEDICATED ARTICLE ANIMAL DRUG LABEL
Date: 20200407

ACTIVE INGREDIENTS: SULFADIMETHOXINE 113.5 g/0.45 kg; ORMETOPRIM 68.1 g/0.45 kg

RofenAid 40

DESCRIPTION

RofenAid
40

Sulfadimethoxine & Ormetoprim

Type A Medicated Article

Antibacterial

Anticoccidial

For use in broiler, replacement (breeder and layer) chickens, turkeys, ducks and chukar partridges only.

Active Drug Ingredients

Sulfadimethoxine . . . . . . . . . . . . . . . . . . . . . . . . . . . . . . . . . . . . . 113.5 grams per pound (25%),

Ormetoprim . . . . . . . . . . . . . . . . . . . . . . . . . . . . . . . . . . . . . . . . . . 68.1 grams per pound (15%)

in a carrier suitable for incorporation in feed.

For use in manufacturing medicated feeds only

Chickens

Broiler and replacement (breeder and layer) chickens

Indications:

As an aid in the prevention of coccidiosis caused by Eimeria tenella, E. necatrix, E. acervulina, E. maxima, E. brunetti and E. mivati; as an aid in the prevention of bacterial infections caused by Haemophilus gallinarum (infectious coryza), Escherichia coli (colibacillosis) and Pasteurella multocida (fowl cholera).

Use directions:

Add 1 lb of RofenAid 40 to one ton of feed to provide 0.02% (113.5 g/ton [0.0125%] sulfadimethoxine and 68.1 g/ton [0.0075%] ormetoprim) concentration in feed. Feed continuously as the sole ration.

Warning:

Do not feed to chickens over 16 weeks (112 days) of age.

Turkeys

Indications:

As an aid in the prevention of coccidiosis caused by Eimeria adenoeides, E. gallopavonis, and E. meleagrimitis; for the prevention of bacterial infections caused by Pasteurella multocida (fowl cholera).

Use directions:

Add 1/2 lb of RofenAid 40 to one ton of feed to provide 0.01% (56.75 g/ton [0.00625%] sulfadimethoxine and 34.05 g/ton [0.00375%] ormetoprim) concentration in feed. Feed continuously as the sole ration.

Ducks

Ducks, including breeding ducks

Indications:

As an aid in the control of bacterial infections due to Pasteurella multocida (fowl cholera) in ducks including breeding ducks.

Use directions:

Add 2 lbs of RofenAid 40 to one ton of feed to provide 0.04% (227 g/ton [0.025%] sulfadimethoxine and 136.2 g/ton [0.015%] ormetoprim) concentration in feed. Medication should be started at the first signs of infection. Feed for 7 days as the sole ration.

Ducks

Indications:

As an aid in the control of bacterial infections due to Escherichia coli, Riemerella anatipestifer (strains 2, 3 & 4) and severe challenge of P. multocida (fowl cholera).

Use directions:

Add 4 lbs of RofenAid 40 to one ton of feed to provide 0.08% (454 g/ton [0.050%] sulfadimethoxine and 272.4 g/ton [0.030%] ormetoprim) concentration in feed. Medication should be started at the first signs of infection. Feed for 7 days as the sole ration.

Caution:

Not for breeding ducks. The safety of feeding sulfadimethoxine and ormetoprim at levels higher than 0.025% and 0.015%, respectively, in breeding ducks has not been established.

Chukar Partridges

Indications:

For the prevention of coccidiosis caused by Eimeria kofoidi and E. legionensis.

Use directions:

Add 1 lb of RofenAid 40 to one ton of feed to provide 0.02% (113.5 g/ton [0.0125%] sulfadimethoxine and 68.1 g/ton [0.0075%] ormetoprim) concentration in feed. Feed continuously as the sole ration to young birds up to 8 weeks of age.

Caution:

The safety of feeding RofenAid 40 to breeding stock has not been established.

Warning

Do not feed to turkeys and ducks producing eggs for food. Withdraw 5 days prior to slaughter of broiler and replacement chickens, turkeys and ducks.

Note

Manufacture of Type B or C feeds from this product requires a Medicated Feed Mill License.
Labels for feeds containing RofenAid 40 must contain appropriate indications, limitations and warnings as well as required feed ingredient information.

Restricted Drug (California) - Use only as directed. Not for human use.
Approved by FDA under NADA # 040-209
Store below 25°C (77°F), excursions permitted to 37°C (99°F).
zoetis
Distributed by:
Zoetis Inc.
Kalamazoo, MI 49007
Product of China
10010602